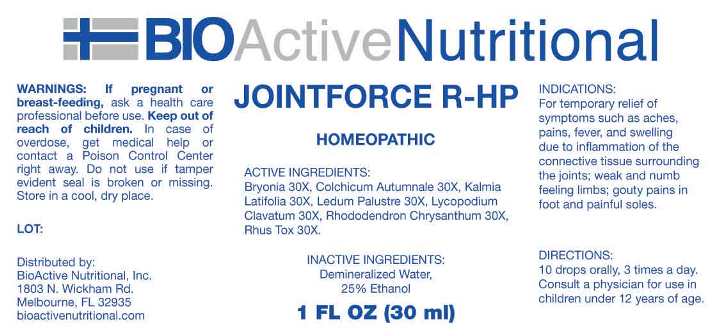 DRUG LABEL: Jointforce R-HP
NDC: 43857-0621 | Form: LIQUID
Manufacturer: BioActive Nutritional, Inc.
Category: homeopathic | Type: HUMAN OTC DRUG LABEL
Date: 20241017

ACTIVE INGREDIENTS: BRYONIA ALBA ROOT 30 [hp_X]/1 mL; COLCHICUM AUTUMNALE BULB 30 [hp_X]/1 mL; KALMIA LATIFOLIA LEAF 30 [hp_X]/1 mL; LEDUM PALUSTRE TWIG 30 [hp_X]/1 mL; LYCOPODIUM CLAVATUM SPORE 30 [hp_X]/1 mL; RHODODENDRON AUREUM LEAF 30 [hp_X]/1 mL; TOXICODENDRON PUBESCENS LEAF 30 [hp_X]/1 mL
INACTIVE INGREDIENTS: WATER; ALCOHOL

DRUG FACTS:

ACTIVE INGREDIENTS:

Bryonia (Alba) 30X, Colchicum Autumnale 30X, Kalmia Latifolia 30X, Ledum Palustre 30X, Lycopodium Clavatum 30X, Rhododendron Chrysanthum 30X, Rhus Tox 30X.

INDICATIONS:

For temporary relief of symptoms such as aches, pains, fever, and swelling due to inflammation of the connective tissue surrounding the joints; weak and numb feeling limbs; gouty pains in foot and painful soles.

WARNINGS:

If pregnant or breast-feeding, ask a health care professional before use.

Keep out of reach of children. In case of overdose, get medical help or contact a Poison Control Center right away.

Do not use if tamper evident seal is broken or missing.

Store in cool, dry place.

Keep out of reach of children. In case of overdose, get medical help or contact a Poison Control Center right away.

DIRECTIONS:

10 drops orally, 3 times a day. Consult a physician for use in children under 12 years of age.

INDICATIONS:

For temporary relief of symptoms such as aches, pains, fever, and swelling due to inflammation of the connective tissue surrounding the joints; weak and numb feeling limbs; gouty pains in foot and painful soles.

INACTIVE INGREDIENTS:

Demineralized water, 25% Ethanol.

QUESTIONS:

Distributed by:
BioActive Nutritional, Inc.
1803 N. Wickham Rd.
Melbourne, FL 32935
bioactivenutritional.com

PACKAGE LABEL DISPLAY:

BIOActive Nutritional
JOINTFORCE R-HP
HOMEOPATHIC
1 FL OZ (30 ml)